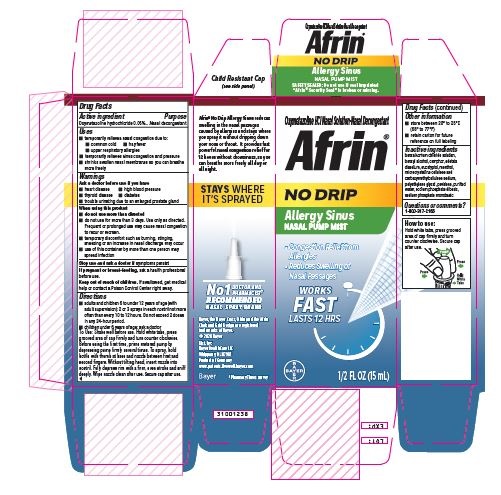 DRUG LABEL: Afrin No-Drip
NDC: 11523-3220 | Form: SPRAY, METERED
Manufacturer: Bayer HealthCare LLC
Category: otc | Type: HUMAN OTC DRUG LABEL
Date: 20251205

ACTIVE INGREDIENTS: OXYMETAZOLINE HYDROCHLORIDE 0.05 mg/1 mL
INACTIVE INGREDIENTS: BENZALKONIUM CHLORIDE; CAMPHOR, (-)-; EDETATE DISODIUM; EUCALYPTOL; MENTHOL; BENZYL ALCOHOL; CARBOXYMETHYLCELLULOSE SODIUM; POVIDONE; SODIUM PHOSPHATE, DIBASIC; SODIUM PHOSPHATE, MONOBASIC; POLYETHYLENE GLYCOL, UNSPECIFIED; CELLULOSE, MICROCRYSTALLINE; WATER

Afrin No-Drip Allergy Sinus

Drug Facts

Active ingredient

Oxymetazoline hydrochloride 0.05%

Purpose

Nasal decongestant

Uses

● temporarily relieves nasal congestion due to:
● common cold ● hay fever
● upper respiratory allergies
● temporarily relieves sinus congestion and pressure

● shrinks swollen nasal membranes so you can breathe more freely

Warnings

Ask a doctor before use if you have

● heart disease ● high blood pressure ● thyroid disease ● diabetes

● trouble urinating due to an enlarged prostate gland

When using this product

● do not use more than directed

● do not use more than 3 days. Use only as directed. Frequent or prolonged use may cause nasal congestion to recur or worsen.

● temporary discomfort may occur such as burning, stinging, sneezing or an increase in nasal discharge may occur

● use of this container by more than one person may spread infection

Stop use and ask a doctor if symptoms persist

PREGNANCY OR BREAST FEEDING

If pregnant or breast-feeding, ask a health professional before use.

Keep out of reach of children. If swallowed, get medical help or contact a Poison Control Center right away.

Directions

· adults and children 6 to under 12 years of age (with adult supervision): 2 or 3 sprays in each nostril not more often than every 10 to 12 hours. Do not exceed 2 doses in any 24 hour period.

· children under 6 years of age: ask a doctor

Shake well before use. Hold white tabs, press grooved area of cap firmly and turn counter clockwise. Before using the first time, prime metered pump by depressing pump firmly several times. To spray, hold bottle with thumb at base and nozzle between first and second fingers. Without tilting head, insert nozzle into nostril. Fully depress rim with a firm, even stroke and sniff deeply. Wipe nozzle clean after use. Secure cap after use.

Other information

· store between 20°C to 25°C (68° to 77°F)

· retain carton for future reference on full labeling

INACTIVE INGREDIENT

Inactive ingredients benzalkonium chloride solution, benzyl alcohol, camphor, edetate disodium, eucalyptol, menthol, microcrystalline cellulose and carboxymethylcellulose sodium, polyethylene glycol, povidone, purified water, sodium phosphate dibasic, sodium phosphate monobasic

Questions or comments? Call 1-800-317-2165

PACKAGE LABEL

Oxymetazoline HCl Nasal Solution-Nasal Decongestant

AFRIN

NoDrip

Won't drip from nose or down throat

Allergy Sinus

Pump Mist

Fast, Powerful

Congestion

Relief from

Allergies

up to 12 Hour Relief

Reduces

Swelling of

Nasal

Passages

#1 Doctor & Pharmacist Recommended Nasal Spray Brand

1/2FL OZ (15mL)